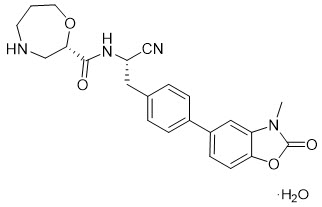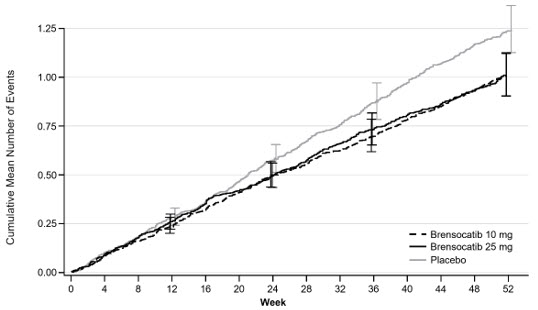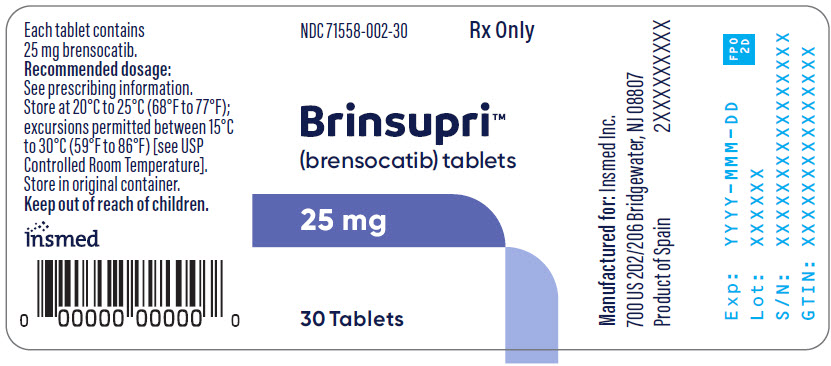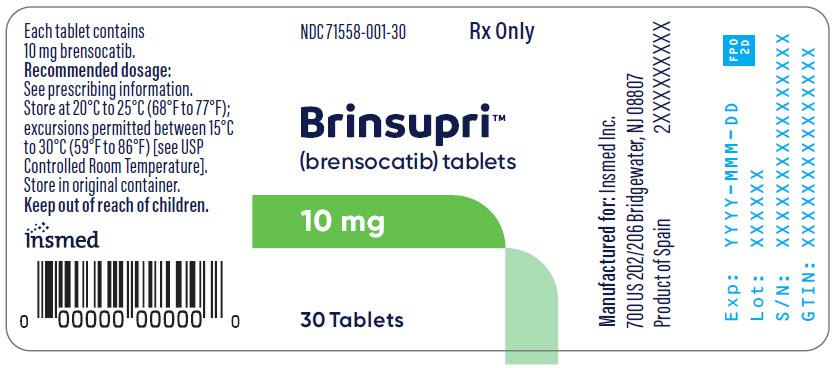 DRUG LABEL: Brinsupri
NDC: 71558-002 | Form: TABLET
Manufacturer: Insmed Incorporated
Category: prescription | Type: HUMAN PRESCRIPTION DRUG LABEL
Date: 20250812

ACTIVE INGREDIENTS: Brensocatib 25 mg/1 1
INACTIVE INGREDIENTS: Microcrystalline Cellulose; Dibasic Calcium Phosphate Dihydrate; SODIUM STARCH GLYCOLATE TYPE A; Silicon Dioxide; Glyceryl Dibehenate

HIGHLIGHTS OF PRESCRIBING INFORMATION

These highlights do not include all the information needed to use BRINSUPRI safely and effectively. See full prescribing information for BRINSUPRI.
BRINSUPRI™ (brensocatib) tablets, for oral use
Initial U.S. Approval: 2025

1 INDICATIONS AND USAGE

BRINSUPRI is a dipeptidyl peptidase 1 (DPP1) inhibitor indicated for the treatment of non-cystic fibrosis bronchiectasis in adult and pediatric patients 12 years of age and older. (1)

2 DOSAGE AND ADMINISTRATION

Recommended dosage: 10 mg or 25 mg orally once daily with or without food. (2.1)

3 DOSAGE FORMS AND STRENGTHS

Tablets: 10 mg and 25 mg (3)

4 CONTRAINDICATIONS

None. (4)

5 WARNINGS AND PRECAUTIONS

Dermatologic Adverse Reactions: Monitor for new rash or skin conditions and refer to dermatology for evaluation. (5.1)

Gingival and Periodontal Adverse Reactions: Gingival and periodontal adverse reactions can occur with BRINSUPRI use. Refer to the dental care services for regular dental checkups and advise patients to perform routine dental hygiene. (5.2)

Live Attenuated Vaccines: It is unknown whether administration of live attenuated vaccines during BRINSUPRI treatment will affect the safety or effectiveness of the vaccines. Avoid use of live attenuated vaccines. (5.3)

6 ADVERSE REACTIONS

Most common adverse reactions (incidence ≥2%): upper respiratory tract infection, headache, rash, dry skin, hyperkeratosis, hypertension. (6.1)

To report SUSPECTED ADVERSE REACTIONS, contact Insmed Incorporated at 1-844-4-INSMED or FDA at 1-800-FDA-1088 or https://www.fda.gov/medwatch.

FULL PRESCRIBING INFORMATION

1 INDICATIONS AND USAGE

BRINSUPRI is indicated for the treatment of non-cystic fibrosis bronchiectasis (NCFB) in adult and pediatric patients 12 years of age and older.

2 DOSAGE AND ADMINISTRATION

2.1 Recommended Dosage

The recommended dosage of BRINSUPRI is as follows:

- 10 mg orally once daily with or without food
  or
- 25 mg orally once daily with or without food

Missed Dose(s)

Patients who miss a dose should take the next dose at their regular time the next day. Do not double the dose to make up for the missed dose.

3 DOSAGE FORMS AND STRENGTHS

Tablets:

- 10 mg, brown, round, film-coated tablets debossed with "10" on one side and "BRE" on the other
- 25 mg, gray, round, film-coated tablets debossed with "25" on one side and "BRE" on the other

4 CONTRAINDICATIONS

None.

5 WARNINGS AND PRECAUTIONS

5.1 Dermatologic Adverse Reactions

Treatment with BRINSUPRI is associated with an increase in dermatologic adverse reactions, including rash, dry skin, and hyperkeratosis [see Adverse Reactions (6.1)]. Monitor patients for development of new rashes or skin conditions and refer patients to a dermatologist for evaluation of new dermatologic findings.

5.2 Gingival and Periodontal Adverse Reactions

Treatment with BRINSUPRI is associated with an increase in gingival and periodontal adverse reactions [see Adverse Reactions (6.1)]. Refer patients to dental care services for regular dental checkups while taking BRINSUPRI. Advise patients to perform routine dental hygiene.

5.3 Live Attenuated Vaccines

The concomitant use of BRINSUPRI and live attenuated vaccines has not been evaluated. It is unknown whether administration of live attenuated vaccines during BRINSUPRI treatment will affect the safety or effectiveness of these vaccines. The use of live attenuated vaccines should be avoided in patients receiving BRINSUPRI.

6 ADVERSE REACTIONS

The following adverse reactions are described elsewhere in the labeling:

- Dermatologic Adverse Reactions [see Warnings and Precautions (5.1)]
- Gingival and Periodontal Adverse Reactions [see Warnings and Precautions (5.2)]

6.1 Clinical Trials Experience

Because clinical trials are conducted under widely varying conditions, adverse reaction rates observed in the clinical trials of a drug cannot be directly compared to rates in the clinical trials of another drug and may not reflect the rates observed in practice.

The safety data below reflect the safety of BRINSUPRI in adult and pediatric patients aged 12 years and older with non-cystic fibrosis bronchiectasis (NCFB). A total of 1721 patients with NCFB were randomized in a double-blind, placebo-controlled clinical trial of 52 weeks duration (ASPEN) [see Clinical Studies (14)]. The safety of BRINSUPRI was based on data from 1719 adult and pediatric patients aged 12 years and older who received at least one dose of BRINSUPRI or placebo. A total of 1156 patients received at least one dose of BRINSUPRI 10 mg or 25 mg orally once daily.

Table 1 shows the adverse reactions occurring at an incidence of ≥2% and higher in BRINSUPRI-treated patients compared to placebo in the safety population from ASPEN.

Table 1 Adverse Reactions with BRINSUPRI with an Incidence of ≥2% and More Common than Placebo in ASPEN
Adverse Reaction | Placebo (N=563) n (%) | BRINSUPRI 10 mg QD (N=582) n (%) | BRINSUPRI 25 mg QD (N=574) n (%)
Upper respiratory tract infection [Upper respiratory tract infection includes coronavirus infection, COVID-19, influenza, upper respiratory tract infection, viral infection, and viral upper respiratory tract infection.] | 141 (25) | 157 (27) | 169 (29)
Headache | 39 (7) | 39 (7) | 49 (9)
Rash [Rash includes rash, rash maculo-papular, rash pruritic, rash erythematous, dermatitis, and erythema.] | 22 (4) | 25 (4) | 35 (6)
Dry skin [Dry skin includes dry skin, chapped lips, cheilitis, lip dry, skin exfoliation, skin fissures, xeroderma, and xerosis.] | 8 (1) | 17 (3) | 25 (4)
Hyperkeratosis [Hyperkeratosis includes hyperkeratosis, palmoplantar keratoderma, and skin hypertrophy.] | 5 (1) | 8 (1) | 16 (3)
Hypertension | 17 (3) | 28 (5) | 13 (2)

Adverse Reactions in WILLOW

A total of 256 adult patients with NCFB were randomized in the 24-week, double-blind, placebo-controlled clinical trial (WILLOW). Of those randomized, 255 adult patients received BRINSUPRI 10 mg, BRINSUPRI 25 mg, or placebo, which consisted of 170 adults treated with at least one dose of BRINSUPRI 10 mg or 25 mg orally once daily. The safety profile for adult patients with NCFB in WILLOW was generally similar to ASPEN, with the exception of a higher incidence of gingival and periodontal adverse reactions. The incidence of gingival and periodontal adverse reactions in WILLOW among patients treated with BRINSUPRI 10 mg and 25 mg were 9.9% and 10.1%, respectively, compared to 2.4% in placebo-treated patients.

Less Common Adverse Reactions

Liver Function Test Elevations

In ASPEN, there was an increase from baseline in average ALT, AST, and alkaline phosphatase levels at all time points from Week 4 through Week 56 in both BRINSUPRI 10 mg and 25 mg arms compared to placebo. The incidence of ALT >3× upper limit of normal (ULN) was 0%, 1.2%, and 0.9%, in patients treated with placebo and BRINSUPRI 10 mg and 25 mg, respectively. The incidence of AST >3× ULN was 0.2%, 0.3%, and 0.5% in patients treated with placebo and BRINSUPRI 10 mg and 25 mg, respectively. The incidence of alkaline phosphatase >1.5× ULN was 2.5%, 4.1%, and 4.0% in patients treated with placebo and BRINSUPRI 10 mg and 25 mg, respectively.

Skin Cancers

In ASPEN, the incidence of skin cancers among patients treated with BRINSUPRI 10 mg and 25 mg was 0.5% and 1.9%, respectively, compared to 1.1% in placebo-treated patients.

Alopecia

In ASPEN, the incidence of alopecia among patients treated with BRINSUPRI 10 mg and 25 mg was 1.5% and 1.6%, respectively, compared to 0.4% in placebo-treated patients.

8 USE IN SPECIFIC POPULATIONS

8.1 Pregnancy

Risk Summary

There are no available data on BRINSUPRI use in pregnant women to evaluate for a drug-associated risk of major birth defects, miscarriage, or other adverse maternal or fetal outcomes.

In animal embryo fetal development (EFD) studies, oral administration of brensocatib to pregnant rats during organogenesis at maternal exposures 128 times the maximum recommended human dose (MRHD) on an AUC basis was associated with malformations. Oral administration of brensocatib to pregnant rabbits during organogenesis demonstrated no adverse developmental effects at doses that produced maternal exposures up to 20 times the MRHD. No adverse development effects were observed after oral administration of brensocatib to pregnant rats from the period of organogenesis through lactation at doses that produced maternal exposures 17 times the MRHD on an AUC basis (see Data).

The estimated background risk of major birth defects and miscarriage for the indicated population is unknown. All pregnancies have a background risk of birth defect, loss, or other adverse outcomes. In the U.S. general population, the estimated background risk of major birth defects and miscarriage in clinically recognized pregnancies is 2% to 4% and 15% to 20%, respectively.

Data

Animal Data

In a rat fertility and EFD study, brensocatib was administered at oral doses of 3, 20, and 100 mg/kg/day to female rats 2 weeks prior to mating, during mating, and through organogenesis until gestation Day 16. The malformation of bent scapula was observed at a maternal dose of 100 mg/kg/day (128 times the MRHD on an AUC basis). There were no adverse findings at maternal oral doses of 20 mg/kg/day (42 times the MRHD on an AUC basis). In a rabbit EFD study, brensocatib was administered at oral doses of 5, 15, or 50 mg/kg/day from gestation Days 7 to 19, a period that covers implantation and major organogenesis. Brensocatib was not associated with adverse effects on the fetus at maternal exposures up to 20 times the MRHD on an AUC basis. Maternal toxicity as indicated by reductions in body weight gain and food consumption was noted at maternal doses of 15 mg/kg/day and greater (greater than 5 times the MRHD on an AUC basis). In a pre- and postnatal development study, oral administration of brensocatib to pregnant rats at doses of 3, 9, or 20 mg/kg/day from gestation Day 6 through lactation Day 20 resulted in no adverse developmental effects in pups at maternal doses up to 20 mg/kg/day (17 times the MRHD on an AUC basis).

8.2 Lactation

Risk Summary

There are no data on the presence of brensocatib and/or its metabolite(s) in human milk, the effects on the breastfed infant, or the effects on milk production.

The developmental and health benefits of breastfeeding should be considered along with the mother's clinical need for BRINSUPRI and any potential adverse effects on the breastfed child from BRINSUPRI or from the underlying maternal condition.

8.4 Pediatric Use

The safety and effectiveness of BRINSUPRI for the treatment of NCFB have been established in pediatric patients aged 12 years and older. Use of BRINSUPRI for this indication is supported by evidence from an adequate and well-controlled trial (ASPEN), which enrolled 41 pediatric patients aged 12 years and older, and additional pharmacokinetic data in pediatric patients aged 12 to 17 years [see Clinical Pharmacology (12.3) and Clinical Studies (14)].

Common adverse reactions in pediatric patients aged 12 years and older enrolled in ASPEN were consistent with those in adults [see Adverse Reactions (6.1)].

The safety and effectiveness of BRINSUPRI have not been established in pediatric patients younger than 12 years of age.

8.5 Geriatric Use

There were 988 patients 65 years of age and older in the clinical studies for non-cystic fibrosis bronchiectasis [see Clinical Studies (14)]. Of the total number of BRINSUPRI-treated patients in these studies, 676 (51%) were 65 years of age and older while 201 (15%) were 75 years of age and older. No observed differences in safety and/or effectiveness in geriatric patients compared to younger adult patients [see Clinical Pharmacology (12.3)].

10 OVERDOSAGE

Consider contacting the Poison Help line (1-800-222-1222) or a medical toxicologist for overdose management recommendations.

11 DESCRIPTION

BRINSUPRI (brensocatib) is a dipeptidyl peptidase 1 (DPP1) inhibitor.

The chemical name for the active ingredient brensocatib monohydrate is (2S)-N-{(1S)-1-cyano-2-[4-(3-methyl-2-oxo-2,3-dihydro-1,3-benzoxazol-5-yl)phenyl]ethyl}-1,4-oxazepane-2-carboxamide monohydrate with a chemical formula of C23H24N4O4 ∙ H2O which corresponds to a molecular weight of 438.48 g/mol. Its structural formula is:

Brensocatib monohydrate drug substance is a white to off-white solid powder. It is slightly soluble at pH 1.2, freely soluble at pH 4.5, and very slightly soluble at pH 6.8 of aqueous media. It is also soluble in acetonitrile and sparingly soluble in ethanol.

BRINSUPRI tablets are available for oral administration in strengths of 10 mg and 25 mg brensocatib with the following inactive ingredients: dibasic calcium phosphate dihydrate, glyceryl dibehenate, microcrystalline cellulose, silicon dioxide, and sodium starch glycolate. The film coating contains ferrosoferric oxide/black iron oxide, iron oxide yellow, and iron oxide red (10 mg) or ferrosoferric oxide/black iron oxide (25 mg), macrogol/PEG, polyvinyl alcohol-partially hydrolyzed, talc, and titanium dioxide.

12 CLINICAL PHARMACOLOGY

12.1 Mechanism of Action

Brensocatib is a competitive, reversible inhibitor of dipeptidyl peptidase 1 (DPP1). DPP1 activates pro-inflammatory neutrophil serine proteases (NSPs) during neutrophil maturation in the bone marrow. Activated NSPs are implicated in the pathogenesis of neutrophil-mediated NCFB inflammation. In cell-based assays, DPP1 inhibition by brensocatib reduces the activity of NSPs including neutrophil elastase, cathepsin G, and proteinase 3.

12.2 Pharmacodynamics

Brensocatib prevents the activation of NSPs via DPP1 inhibition resulting in decreases in NSP activity in patients. In exploratory assays, brensocatib was associated with dose-dependent reductions in NSP activity in patients with NCFB.

Cardiac Electrophysiology

At concentrations approximately 2 times the steady state peak concentration of the maximum recommended daily dose of brensocatib in adult and adolescents with NCFB, clinically significant QTc interval prolongation was not observed.

12.3 Pharmacokinetics

Following once daily administration of brensocatib 10 mg, the estimated geometric mean (CV%) Cmax is 85.4 ng/mL (33%) and AUCtau is 1360 ng*h/mL (41%). Following once daily administration of brensocatib 25 mg, the estimated geometric mean (CV%) Cmax is 259 ng/mL (31%) and AUCtau is 4060 ng*h/mL (39%).

Brensocatib Cmax and AUCtau increase in a greater than dose proportional manner between doses of 10 mg and 1.6 times the highest recommended dose. Between doses of 10 mg and 1.6 times the highest recommended dose brensocatib once daily, brensocatib geometric mean steady state Cmax increased by 5.1-fold and AUCtau increased by 5.3-fold. In healthy subjects, at steady state, Cmax increased by about 1.5-fold and AUCtau increased by about 2-fold when compared to those observed following a single dose.

No clinically relevant differences in brensocatib pharmacokinetics were observed between healthy subjects and patients with NCFB.

Absorption

The absolute oral bioavailability of brensocatib has not been studied in humans. Based on data from a mass balance study in healthy subjects, the oral absorption of brensocatib in humans is greater than 80%. Following a single dose of 10 mg or 25 mg brensocatib, the median (min, max) time to maximum plasma concentration (Tmax) is 1.0-1.4 hours (0.5, 3.0 hours).

Effect of Food

No clinically relevant differences in brensocatib pharmacokinetics were observed following administration of brensocatib with a high-fat meal (990 calories, 52% fat).

Distribution

Following once daily administration of 10 mg or 25 mg brensocatib in patients with NCFB, the estimated volume of distribution at steady state ranged from 126 to 138 L. The protein binding of brensocatib in human plasma was 87.2%.

Elimination

Following a single oral administration of brensocatib at 10 mg or 25 mg in healthy subjects, the elimination half-life ranged from 25 to 39 hours and the apparent oral clearance ranged from 6.4 to 10.7 L/hour.

Metabolism

Brensocatib is primarily metabolized by CYP3A and to a lesser extent by CYP2C8 and CYP2D6. Brensocatib accounted for 16.2% of the total radioactivity in plasma. One major circulating metabolite, thiocyanate, was identified in plasma and accounted for 51% of the total radioactivity AUC following administration of a radio-labeled brensocatib dose. In patients with NCFB at recommended doses of brensocatib, no clinically meaningful changes of plasma thiocyanate from baseline were observed.

Excretion

Following administration of a single oral dose of radiolabeled brensocatib 1.6 times the highest recommended dose to healthy subjects, 54.2% of dose was recovered in urine (22.8% as unchanged brensocatib) and 28.3% of dose was recovered in feces (2.4% as unchanged brensocatib).

Specific Populations

No clinically significant differences in the pharmacokinetics of brensocatib were observed based on age (12 to 85 years), sex, race (72% White, 6% Black, and 12% Asian), or body weight (32 to 155 kg).

No clinically significant differences in the pharmacokinetics of brensocatib were observed based on mild, moderate, or severe renal impairment (eGFR 15-89 mL/min/1.73 m^2); or mild, moderate, or severe hepatic impairment (Child-Pugh Class A, B, or C).

Drug Interaction Studies

Clinical Studies and Model-Informed Approaches

Strong CYP3A4 and P-gp Inhibitors: Brensocatib Cmax increased by 68% and AUC increased by 55% following concomitant administration with clarithromycin (a strong CYP3A4 and P-gp inhibitor) 500 mg twice daily for 6 days.

Moderate CYP3A4 and P-gp Inhibitors: Brensocatib Cmax increased by 53% and AUC increased by 32% following concomitant administration with verapamil (a moderate CYP3A4 and P-gp inhibitor) 240 mg once daily for 5 days.

Strong CYP3A4 Inducers: Brensocatib Cmax decreased by 15% and AUC decreased by 33% following concomitant administration with rifampin (a strong CYP3A4 inducer) 600 mg once daily for 9 days.

Acid-Reducing Agents: Brensocatib Cmax and AUC were unchanged following concomitant administration with esomeprazole (a proton-pump inhibitor) 40 mg once daily for 4 days.

CYP3A4 Substrates: No clinically significant differences in the pharmacokinetics of midazolam (a sensitive CYP3A4 substrate) are predicted when used concomitantly with brensocatib.

In Vitro Studies

CYP450 Enzymes: Brensocatib is a substrate of CYP3A. Brensocatib does not inhibit CYP1A2, CYP2B6, CYP2C8, CYP2C9, CYP2C19, CYP2D6, or CYP3A. Brensocatib is a weak CYP3A inducer, but not an inducer of CYP1A2, CYP2B6, CYP2C8, CYP2C9, or CYP2C19.

Transporter Systems: Brensocatib is a substrate of P-glycoprotein (P-gp) and breast cancer resistance protein (BCRP), but is not a substrate of MATE1, MATE2-K, OAT1, OAT3, OATP1B1, OATP1B3, OCT1, and OCT2. Brensocatib is an inhibitor of BCRP, OATP1B, MATE1, and MATE2-K, but is not an inhibitor of P-gp, OAT1, OCT2, OAT3, or OATP1B3.

13 NONCLINICAL TOXICOLOGY

13.1 Carcinogenesis, Mutagenesis, Impairment of Fertility

A two-year study in Han Wistar rats and a 6-month study in Tg.rasH2 transgenic mice were conducted to assess the carcinogenic potential of brensocatib. No evidence of tumorigenicity was observed in male or female rats at an exposure approximately 56 times the MRHD on an AUC basis. No evidence of tumorigenicity was observed in male and female Tg.rasH2 mice at oral doses up to 50 mg/kg/day, the highest dose tested. Brensocatib was negative for genotoxicity in the following assays: in vitro bacterial reverse mutation (Ames) assay, in vitro mouse lymphoma mutation assay, and in vivo micronucleus assay in rats.

Oral administration of brensocatib to male and female rats at up to 50 and 100 mg/kg/day, respectively, had no adverse effects on fertility and reproductive performance indices (150 and 231 times the MRHD on an AUC basis, respectively).

14 CLINICAL STUDIES

The efficacy of BRINSUPRI was evaluated in two randomized, double-blind, placebo-controlled, parallel-group, multicenter, multinational clinical trials (ASPEN [NCT04594369] and WILLOW [NCT03218917]).

ASPEN was a 52-week trial that included 1721 adult and pediatric patients 12 years of age and older with NCFB (1680 adults and 41 pediatric patients 12 years of age to less than 18 years of age) who were randomized to BRINSUPRI 10 mg (n=583), BRINSUPRI 25 mg (n=575), or placebo (n=563) administered orally once daily.

WILLOW was a 24-week trial that included 256 adult patients with NCFB who were randomized to BRINSUPRI 10 mg (n=82), BRINSUPRI 25 mg (n=87), or placebo (n=87) administered orally once daily.

In both ASPEN and WILLOW, all adult patients had a history of confirmed NCFB by chest computed tomography with at least 2 documented pulmonary exacerbations (PEx) prior to screening in the past 12 months. In ASPEN, pediatric patients 12 years of age and older had at least one PEx in the prior 12 months.

Demographics and baseline characteristics of patients in ASPEN and WILLOW are provided in Table 2.

Table 2 Demographics and Baseline Characteristics of Patients in ASPEN and WILLOW
 | ASPEN (N=1721) | WILLOW (N=256)
Age (years), mean (SD) | 60 (16) | 64 (12)
Female n (%) | 1107 (64) | 174 (68)
White n (%) | 1266 (74) | 225 (88)
Black or African American n (%) | 10 (1) | 4 (2)
Asian n (%) | 191 (11) | 23 (9)
Hispanic or Latino n (%) | 511 (30) | 6 (2)
≥3 PEx in prior 12 months n (%) | 502 (29) | 84 (33)
Former smoker n (%) | 510 (30) | 86 (34)
ppFEV1 post-bronchodilator, mean (SD) | 74 (23) | 68 (24)
Sputum positive for Pseudomonas aeruginosa n (%) | 607 (35) | 89 (35)
Chronic macrolide therapy n (%) | 329 (19) | 40 (16)
Abbreviations: N, number of patients in the intent-to-treat analysis set; n, number of patients; PEx, pulmonary exacerbations; pp, percent predicted; FEV1, forced expiratory volume in 1 second; SD, standard deviation

ASPEN

The primary efficacy endpoint in ASPEN was the annualized rate of PEx over the 52-week treatment period.

Pulmonary exacerbations were defined as worsening of 3 or more of the following major symptoms over 48 hours: increased cough, increased sputum volume or change in sputum consistency, increased sputum purulence, increased breathlessness, decreased exercise tolerance, fatigue and/or malaise, and hemoptysis, resulting in a healthcare provider's decision to prescribe systemic antibiotics. Pulmonary exacerbations were considered severe if requiring treatment with intravenous antibacterial drugs and/or resulted in hospitalization.

Treatment with BRINSUPRI 10 mg or 25 mg in patients with NCFB demonstrated reductions in the mean rate of PEx over 52 weeks compared with placebo (Figure 1). Table 3 provides the results of the annualized rate of PEx, and the results of the key secondary endpoints in ASPEN of time to first PEx, proportion of patients remaining exacerbation free throughout the 52-week treatment period, annualized rate of severe PEx, and the change from baseline in post-bronchodilator FEV1.

Table 3 Primary and Key Secondary Efficacy Analyses of Pulmonary Exacerbations and FEV1 Over 52 Weeks in ASPEN
 | Placebo (N=563) | BRINSUPRI 10 mg (N=583) | BRINSUPRI 25 mg (N=575)
Annualized Rate of PEx | 1.29 | 1.02 | 1.04
Rate Ratio (95% CI) | -- | 0.79 (0.68, 0.92) | 0.81 (0.69, 0.94)
Median Time to First PEx (weeks) | 36.71 | 49.00 | 50.71
Hazard Ratio (95% CI) | -- | 0.81 (0.70, 0.95) | 0.83 (0.70, 0.97)
Proportion of Patients that were PEx Free at Week 52 (%) | 40.3 | 48.5 | 48.5
Odds Ratio (95% CI) | -- | 1.41 (1.11, 1.81) | 1.40 (1.10, 1.79)
Annualized Rate of Severe PEx | 0.19 | 0.14 | 0.14
Rate Ratio (95% CI) | -- | 0.74 (0.51, 1.09) | 0.74 (0.52, 1.06)
LS Mean Change from Baseline in Post-Bronchodilator FEV1 (mL) at Week 52 | -62 | -50 | -24
Difference vs Placebo (95% CI) | -- | 11 (-14, 37) | 38 (11, 65)
Abbreviations: FEV1, forced expiratory volume in 1 second; LS, least squares; PEx, pulmonary exacerbation

Figure 1 Cumulative Mean Number of Pulmonary Exacerbations through Week 52

WILLOW

The primary efficacy endpoint in WILLOW was the time to first PEx over the 24-week treatment period. The time to first PEx was longer for patients receiving BRINSUPRI 10 mg and 25 mg compared to placebo (hazard ratio BRINSUPRI 10 mg and 25 mg versus placebo; 0.58 and 0.62, respectively; 95% CI: 0.35 to 0.95 and 0.38 to 0.99, respectively).

16 HOW SUPPLIED/STORAGE AND HANDLING

BRINSUPRI (brensocatib) tablets are supplied as described in Table 4:

Table 4 BRINSUPRI Tablets and Package Configuration
Strength | Tablet Description | Package Configuration | NDC
10 mg | brown, round, film-coated tablets debossed with "10" on one side and "BRE" on the other | bottles of 30 tablets | 71558-001-30
25 mg | gray, round, film-coated tablets debossed with "25" on one side and "BRE" on the other | bottles of 30 tablets | 71558-002-30

STORAGE AND HANDLING

Store at 20°C to 25°C (68°F to 77°F); excursions permitted between 15°C to 30°C (59°F to 86°F) [see USP Controlled Room Temperature]. Store in original container.

17 PATIENT COUNSELING INFORMATION

Advise the patient to read the FDA-approved patient labeling (Patient Information).

Dermatologic Adverse Reactions

Inform patients that BRINSUPRI is associated with a risk of adverse skin reactions including rash, dry skin, and hyperkeratosis. Advise patients to monitor their skin and report any new rash or skin condition [see Warnings and Precautions (5.1)].

Gingival and Periodontal Adverse Reactions

Inform patients that BRINSUPRI is associated with a risk of gingival and periodontal adverse reactions. Advise patients to have regular dental checkups while taking BRINSUPRI. Advise patients to perform routine dental hygiene [see Warnings and Precautions (5.2)].

Live Attenuated Vaccines

Instruct patients to inform the healthcare provider that they are taking BRINSUPRI prior to a potential vaccination [see Warnings and Precautions (5.3)].

Manufactured for:
Insmed Incorporated
Bridgewater, NJ 08807

© Insmed Incorporated 2025
BRINSUPRI and Insmed are trademarks of Insmed Incorporated.
For patent information: https://insmed.com/program-patents/
For more information, go to www.BRINSUPRI.com or call 1-844-4-INSMED (1-844-446-7633).

Patient Information
BRINSUPRI (brin-SOO-pree)
(brensocatib)
tablets, for oral use

What is BRINSUPRI?
BRINSUPRI is a prescription medicine used to treat non-cystic fibrosis bronchiectasis (NCFB) in adults and children 12 years of age and older. It is not known if BRINSUPRI is safe and effective in children under 12 years of age.

Before taking BRINSUPRI, tell your healthcare provider about all of your medical conditions, including if you:

- have recently received or are scheduled to receive any live attenuated vaccinations.
- are pregnant or plan to become pregnant. It is not known if BRINSUPRI will harm your unborn baby.
- are breastfeeding or plan to breastfeed. It is not known if BRINSUPRI passes into your breast milk. Talk to your healthcare provider about the best way to feed your baby during this time.

Tell your healthcare provider about all the medicines you take, including prescription and over-the-counter medicines, vitamins, and herbal supplements. Do not change or stop your medicines unless your healthcare provider tells you to.

How should I take BRINSUPRI?

- Take BRINSUPRI exactly as your healthcare provider tells you to take it.
- Take 1 BRINSUPRI tablet by mouth daily with or without food.
- If you forget to take a dose of BRINSUPRI, take your next dose at your regular time the next day.
- Do not double the dose to make up for the missed dose.

What are the possible side effects of BRINSUPRI?
BRINSUPRI may cause serious side effects including:

- Skin problems. Tell your healthcare provider about any new skin symptoms. Your healthcare provider may send you to a dermatologist for an examination if needed.
- Dental problems. Get regular dental checkups while taking BRINSUPRI. Brush and clean your teeth as recommended by your dentist. Tell your healthcare provider and contact your dentist if you experience new gum (gingival) or teeth (dental) symptoms.

Common side effects of BRINSUPRI include:

- upper respiratory tract infection
- headache
- rash

- dry skin
- small areas of skin thickening (hyperkeratosis)
- high blood pressure (hypertension)

Less common side effects include abnormal liver blood test, hair loss (alopecia), and skin cancers.
These are not all of the possible side effects of BRINSUPRI.
Call your doctor for medical advice about side effects. You may also report side effects to FDA at 1-800-FDA-1088 or www.fda.gov/medwatch.

How should I store BRINSUPRI?

- Store BRINSUPRI at room temperature between 68°F to 77°F (20°C to 25°C).
- Keep BRINSUPRI in its original bottle.

Keep BRINSUPRI and all medicines out of the reach of children.

General information about the safe and effective use of BRINSUPRI
Medicines are sometimes prescribed for purposes other than those listed in a Patient Information leaflet. Do not use BRINSUPRI for a condition for which it was not prescribed. Do not give BRINSUPRI to other people, even if they have the same symptoms that you have. It may harm them. You can ask your pharmacist or healthcare provider for information about BRINSUPRI that is written for health professionals.

What are the ingredients in BRINSUPRI?
Active ingredient: brensocatib monohydrate
Inactive ingredients: dibasic calcium phosphate dihydrate, glyceryl dibehenate, microcrystalline cellulose, silicon dioxide, and sodium starch glycolate
Film coating: ferrosoferric oxide/black iron oxide, iron oxide yellow, and iron oxide red or ferrosoferric oxide/black iron oxide, macrogol/PEG, polyvinyl alcohol-partially hydrolyzed, talc, and titanium dioxide

Manufactured for: Insmed Incorporated, Bridgewater, NJ 08807
© Insmed Incorporated 2025
BRINSUPRI and Insmed are trademarks of Insmed Incorporated.
For patent information: https://insmed.com/program-patents/
For more information, go to www.BRINSUPRI.com or call 1-844-4-INSMED (1-844-446-7633).

This Patient Information has been approved by the U.S. Food and Drug Administration

Issued: 08/2025

PRINCIPAL DISPLAY PANEL - 25 mg Tablet Bottle Label

NDC 71558-002-30
Rx Only

Brinsupri™
(brensocatib) tablets

25 mg

30 Tablets

PRINCIPAL DISPLAY PANEL - 10 mg Tablet Bottle Label

NDC 71558-001-30
Rx Only

Brinsupri™
(brensocatib) tablets

10 mg

30 Tablets